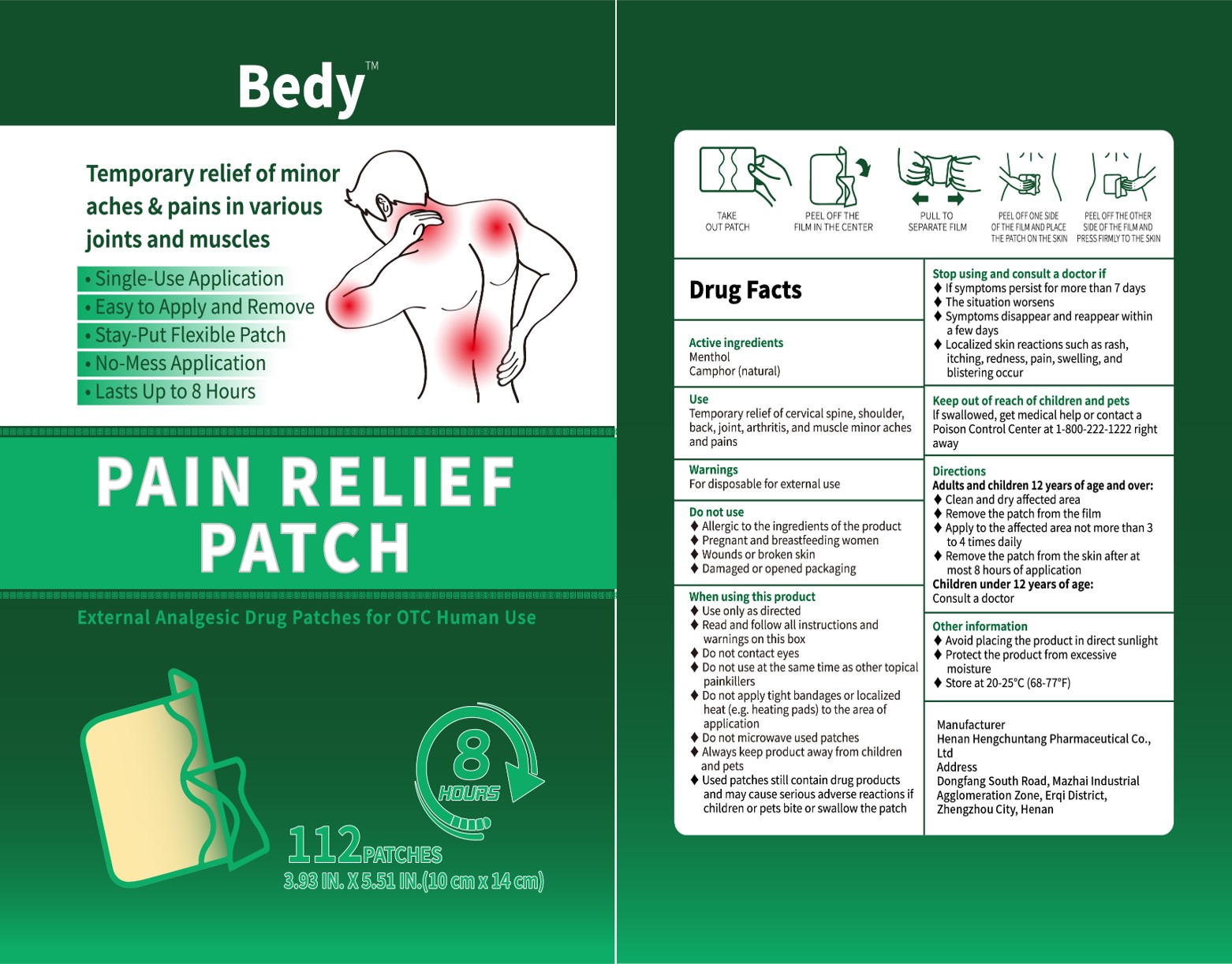 DRUG LABEL: PAIN RELIEF
NDC: 85152-001 | Form: PATCH
Manufacturer: Henan Hengchuntang Pharmaceutical Co., Ltd
Category: otc | Type: HUMAN OTC DRUG LABEL
Date: 20250119

ACTIVE INGREDIENTS: MENTHOL 2 g/10 g; CAMPHOR (NATURAL) 1 g/10 g
INACTIVE INGREDIENTS: ETHYLENE-VINYL ACETATE COPOLYMER (28% VINYL ACETATE); COTTON

Active ingredients

Menthol

Camphor (natural)

Purpose

Temporary relief of minoraches & pains in variousjoints and muscles.

Single-Use Application

Easy to Apply and Remove.

Stay-Put Flexible Patch

No-Mess Application

Lasts Up to 8 Hours

Use

When using this productUse only as directed

◆Read and follow all instructions andwarnings on this box

◆ Do not contact eyes

◆ Do not use at the same time as other topicalpainkillers
Do not apply tight bandages or localizedheat (e.g. heating pads) to the area ofapplicationDo not microwave used patches

◆Always keep product away from childrenand petsUsed patches still contain drug productsand may cause serious adverse reactions ifchildren or pets bite or swallow the patch

Inactive ingredient

EVA-28

COTTON

Do not use

Allergic to the ingredients of the produc

tPregnant and breastfeeding women Wounds or broken skin

◆Damaged or opened packaging

Stop using

Stop using and consult a doctor if◆lf symptoms persist for more than 7 daysThe situation worsensSymptoms disappear and reappear withina few daysLocalized skin reactions such as rash,itching, redness, pain, swelling, andblistering occur

Keep out of reach of children and petslf swallowed, get medical help or contact aPoison Control Center at 1-800-222-1222 rightaway

Dosage

DirectionsAdults and children 12 years of age and over:Clean and dry affected areaRemove the patch from the filmApply to the affected area not more than 3to 4 times dailyRemove the patch from the skin after atmost 8 hours of applicationChildren under 12 years of age:Consult a doctor

Warnings

WarningsFor disposable for external use

Directions

DirectionsAdults and children 12 years of age and over:Clean and dry affected areaRemove the patch from the filmApply to the affected area not more than 3to 4 times dailyRemove the patch from the skin after atmost 8 hours of applicationChildren under 12 years of age:Consult a doctor